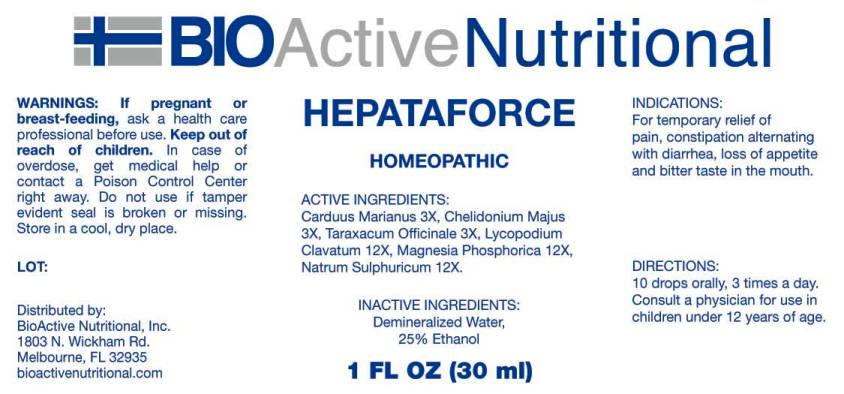 DRUG LABEL: Hepataforce
NDC: 43857-0231 | Form: LIQUID
Manufacturer: BioActive Nutritional
Category: homeopathic | Type: HUMAN OTC DRUG LABEL
Date: 20160719

ACTIVE INGREDIENTS: MILK THISTLE 3 [hp_X]/1 mL; CHELIDONIUM MAJUS 3 [hp_X]/1 mL; TARAXACUM OFFICINALE 3 [hp_X]/1 mL; LYCOPODIUM CLAVATUM SPORE 12 [hp_X]/1 mL; MAGNESIUM PHOSPHATE, DIBASIC TRIHYDRATE 12 [hp_X]/1 mL; SODIUM SULFATE 12 [hp_X]/1 mL
INACTIVE INGREDIENTS: WATER; ALCOHOL

Drug Facts:

ACTIVE INGREDIENTS:

Carduus Marianus 3X, Chelidonium Majus 3X, Taraxacum Officinale 3X, Lycopodium Clavatum 12X, Magnesia Phosphorica 12X, Natrum Sulphuricum 12X.

INDICATIONS:

For temporary relief of pain, constipation alternating with diarrhea, loss of appetite and bitter taste in the mouth.

WARNINGS:

If pregnant or breast-feeding, ask a health care professional before use.

Keep out of reach of children. In case of overdose, get medical help or contact a Poison Control Center right away.

Do not use if tamper evident seal is broken or missing.

Store in a cool, dry place.

Keep out of reach of children. In case of overdose, get medical help or contact a Poison Control Center right away.

DIRECTIONS:

10 drops orally, 3 times a day. Consult a physician for use in children under 12 years of age.

INDICATIONS:

For temporary relief of pain, constipation alternating with diarrhea, loss of appetite and bitter taste in the mouth.

INACTIVE INGREDIENTS:

Demineralized Water, 25% Ethanol

QUESTIONS:

Distributed by:
BioActive Nutritional, Inc.
1803 N. Wickham Rd.
Melbourne, FL 32935
bioactivenutritional.com

PACKAGE LABEL DISPLAY:

BIOActive Nutritional

HEPATAFORCE

HOMEOPATHIC

1 FL OZ (30 ml)